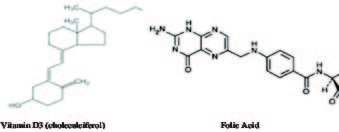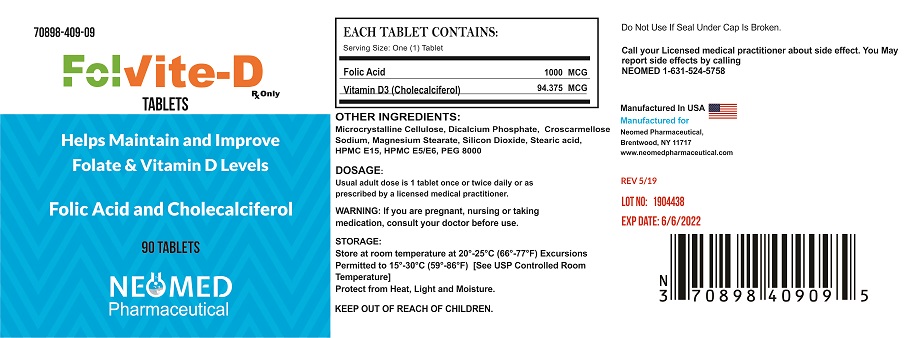 DRUG LABEL: FOLVITE-D
NDC: 70898-409 | Form: TABLET, COATED
Manufacturer: NEOMED PHARMACEUTICAL
Category: other | Type: DIETARY SUPPLEMENT
Date: 20190613

ACTIVE INGREDIENTS: FOLIC ACID 1 mg/1 1; CHOLECALCIFEROL 3775 [iU]/1 1
INACTIVE INGREDIENTS: MICROCRYSTALLINE CELLULOSE; ANHYDROUS DIBASIC CALCIUM PHOSPHATE; CROSCARMELLOSE SODIUM; MAGNESIUM STEARATE; SILICON DIOXIDE; STEARIC ACID; HYPROMELLOSES; POLYETHYLENE GLYCOL 8000

FOLVITE-D

DESCRIPTION

FOLVITE-D tablet is an orally administered prescription strength folate product for the dietary management of patients with unique nutritional needs requiring increased folate levels, Vitamin D levels, or used in improving the nutritional status of patients with folic acid and vitamin D deficiency. FOLVITE-D should be administered under the supervision of a licensed medical practitioner. Vitamin D3 (cholecalciferol) is a white, crystalline powder, very soluble in water. Folic acid occurs as a yellow or yellowishorange crystalline powder and is very soluble in water and insoluble in alcohol. The structural formula of Vitamin D3 and folic acid are as follows:

Each Tablet Contains:
Folic Acid | 1000 MCG
Vitamin D3 (Cholecalciferol) | 94.375 MCG

Each tablet contains the following inactive ingredients: Microcrystalline Cellulose, Dicalcium Phosphate, Croscarmellose Sodium, Magnesium Stearate, Silicon Dioxide, Stearic acid, HPMC E15, HPMC E5/E6, PEG 8000.

INDICATIONS AND USAGE

FOLVITE-D is indicated for dietary management of patients with unique nutritional needs requiring increased folate levels, Vitamin D levels, or used in improving the nutritional status of patients with folic acid and vitamin D deficiency.

DOSAGE:
Usual adult dose is 1 tablet once or twice daily or as prescribed by a licensed medical practitioner.

------------------------------------------------------------------------------------------------------------------------------------------

This statement has not been evaluated by the FDA. This product is not intended to diagnose, treat, cure, or prevent disease.

CLINICAL PHARMACOLOGY

The in vivo synthesis of the major biologically active metabolites of vitamin D occurs in two steps. The first hydroxylation of Vitamin D takes place in the liver (to 25-hydroxyvitamin D) and the second in the kidneys (to 1, 25-dihydroxyvitamin D). Vitamin D metabolites promote the active absorption of calcium and phosphorus by the small intestine, thus elevating serum calcium and phosphate levels sufficiently to permit bone mineralization. Vitamin D metabolites also mobilize calcium and phosphate from bone and probably increase the reabsorption of calcium and perhaps also of phosphate by the renal tubules.

There is a time lag of 10 to 24 hours between the administration of vitamin D and the initiation of its action in the body due to the necessity of synthesis of the active metabolites in the liver and kidneys. Parathyroid hormone is responsible for the regulation of this metabolism in the kidneys.

Folic acid is the precursor of tetrahydrofolic acid, which is involved as a cofactor for transformylation reactions in the biosynthesis of purines and thymidylates of nucleic acids. Impairment of thymidylate synthesis in patients with folic acid deficiency is thought to account for the defective deoxyribonucleic acid (DNA) synthesis that leads to megaloblast formation and megaloblastic and macrocytic anemias.

Folic acid is absorbed rapidly from the small intestine, primarily from the proximal portion. Naturally occurring conjugated folates are reduced enzymatically to folic acid in the gastrointestinal tract prior to absorption. Folic acid appears in the plasma approximately 15 to 30 minutes after an oral dose; peak levels are generally reached within 1 hour.

CONTRAINDCATIONS

This product is contraindicated in patients with a known hypersensitivity to any of the ingredients. FOLVITE-D is contraindicated in patients with hypercalcemia, malabsorption syndrome, abnormal sensitivity to the toxic effects of vitamin D, and hypervitaminosis D.

WARNINGS AND PRECAUTIONS

KEEP OUT OF THE REACH OF CHILDREN. In case of an accidental overdose, call a doctor or a poison control center immediately.

Tell your doctor if you have: kidney problems or thyroid disease.

This medication should be used as directed by your physician during pregnancy or while breastfeeding. Consult your doctor about the risks and benefits.

Folic acid alone is improper therapy in the treatment of pernicious anemia and other megaloblastic anemias where vitamin B12 is deficient. Folic acid in doses above 0.1 mg daily may obscure pernicious anemia in that hematologic remission can occur while neurological manifestations progress.

Folic acid alone is improper therapy in the treatment of pernicious anemia and other megaloblastic anemias where vitamin B12 is deficient. Folic acid in doses above 0.1 mg daily may obscure pernicious anemia in that hematologic remission can occur while neurological manifestations progress.

There is evidence that the anticonvulsant action of phenytoin is antagonized by folic acid. A patient whose epilepsy is completely controlled
by phenytoin may require increased doses to prevent convulsions if folic acid is given.

ADVERSE REACTIONS

Allergic sensitization has been reported following both oral and parenteral administration of folic acid.

Call your doctor if you experience any of the following rare but possible signs of hypervitaminosis D: nausea, vomiting, constipation, loss of appetite, increased thirst, increased urination, mental/mood changes or unusual tiredness.

You should call your doctor for medical advice about serious adverse events. To report adverse side effects or to obtain product information, contact Neomed pharmaceutical, at 16315245758

HOW SUPPLIED

FOLVITE-D tablets are dispensed in bottles of 90ct (70898-409-09)
FOLVITE-D tablets are clear coated and caplet shaped tablets

All prescriptions using this product shall be pursuant to state statutes as applicable. This product is an Rx only and may be administered only under a physician's supervision. There are no implied or explicit claims on therapeutic equivalence.
STORAGE
KEEP OUT OF THE REACH OF CHILDREN
Store at 20°-25°C (66°-77°F); excursions permitted to 15°-30°C (59°-86°F) [See USP Controlled Room Temperature.] Protect from heat, light and moisture.

Manufactured for:
Neomed Pharmaceutical
Brentwood, NY 11717